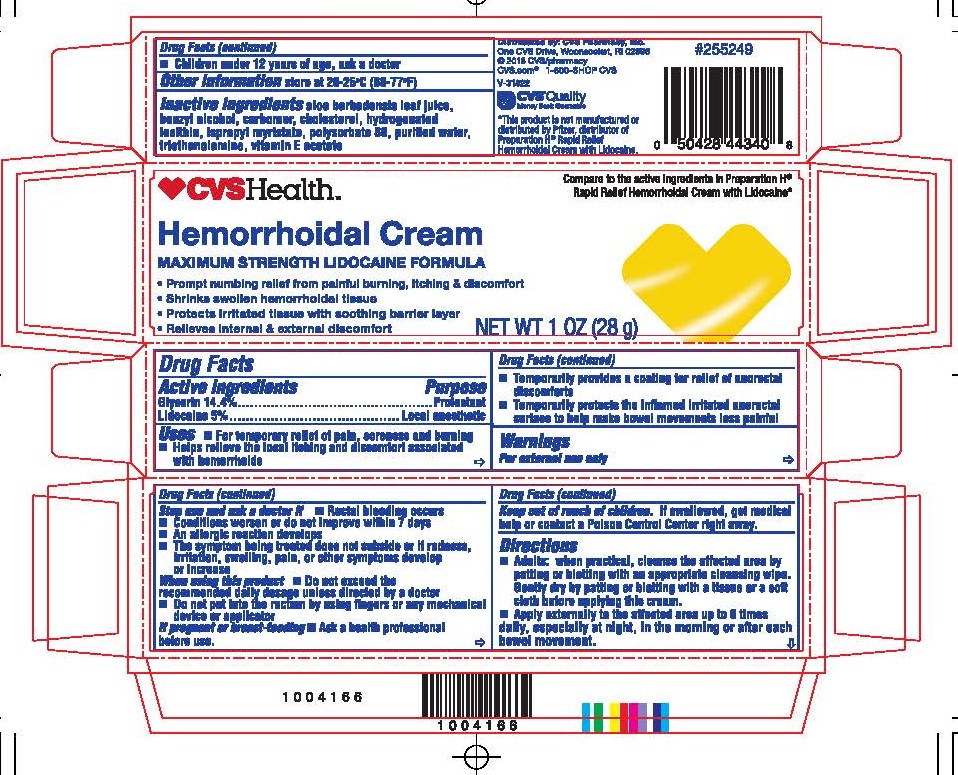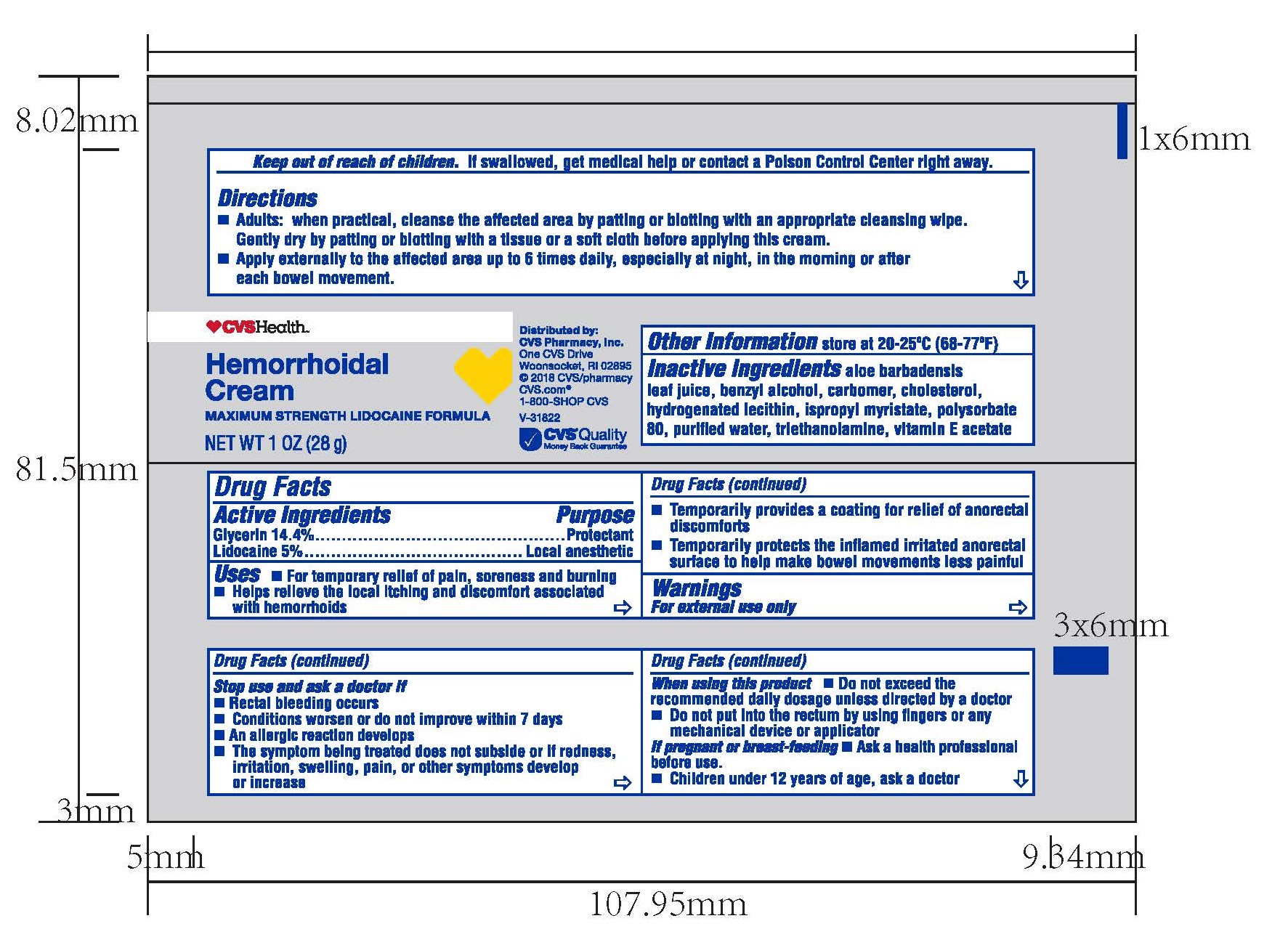 DRUG LABEL: Hemorrhoidal Relief Cream
NDC: 51316-333 | Form: CREAM
Manufacturer: CVS Pharmacy, Inc
Category: otc | Type: HUMAN OTC DRUG LABEL
Date: 20211008

ACTIVE INGREDIENTS: GLYCERIN 4.032 g/28 g; LIDOCAINE 1.4 g/28 g
INACTIVE INGREDIENTS: ALOE VERA LEAF; BENZYL ALCOHOL; CARBOMER HOMOPOLYMER TYPE C; CHOLESTEROL; HYDROGENATED SOYBEAN LECITHIN; ISOPROPYL MYRISTATE; POLYSORBATE 80; WATER; ALPHA-TOCOPHEROL ACETATE

CVS Health Hemorrhoidal Cream Maximum Strength Lidocaine Formula

Uses

- For temporary relief of pain, soreness and burning
- Helps relieve the local itching and discomfort associated with hemorrhoids
- Temporarily provides a coasting for relief of anorectal discomforts
- Temporarily portects the inflamed irritated anorectal surface to help make bowel movements less painful

Warnings

For External use only

Directions

- Adults: when practical, cleanse the affected area by patting or blotting with an appropriate cleansing wipe. Gently dry by patting or blotting with a tissue or a soft cloth before applying this cream.
- Apply externally to the affected area up to 6 times daily, especially at night, in the morning or after each bowel movement.
- Children under 12 years of age, ask a doctor

INACTIVE INGREDIENT

Inactive ingredients: Aloe Barbadensis Leaf Juice, Benzyl Alcohol, Carbomer, Cholesterol, Hydrogenated Lecithin, Isopropyl Myristate, Polysorbate 80, Purified Water, Triethanolamine, vitamin E Acetate

Active Ingredients Purpose
Lidocaine 5%...............................Local anesthetic
Glycerin 14.4%............................Protectant

PURPOSE

Protectant

Local anesthetic

Keep out of reach of children. If swallowed get medical help or contact a Poison Control Center right away.

If pregnant or breast-feeding

- Ask a health professional before use.

Stop use and ask a doctor if

- Rectal bleeding occurs
- Condition worsens or does not improve within 7 days
- An allergic reaction occurs
- The symptom being treated does not subside or if redness, irritation, swelling, pain, or other symptoms develop or increase

Ask a doctor or pharmacist before use if you are presently taking a prescription drug for high blood pressure or depression.

If pregnant or breast-feeding, ask a health professional before use.

When using this product

- Do not exceed the recommended daily dosage unless directed by a doctor
- Do not put this product into the rectum by using fingers or any mechanical device or applicator